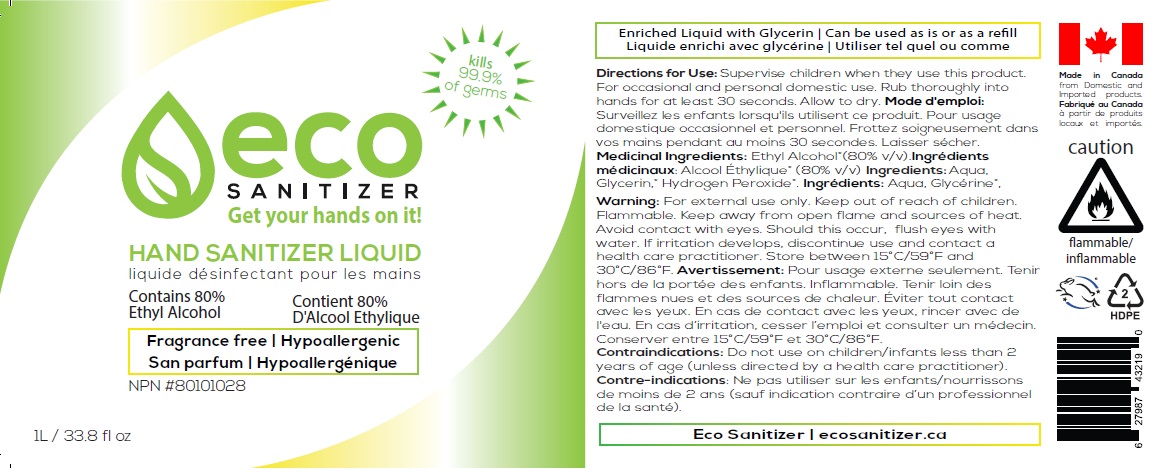 DRUG LABEL: Eco Sanitizer Liquid
NDC: 80731-001 | Form: LIQUID
Manufacturer: 0966452 B.C. Ltd.
Category: otc | Type: HUMAN OTC DRUG LABEL
Date: 20201012

ACTIVE INGREDIENTS: ALCOHOL 80 mL/100 mL
INACTIVE INGREDIENTS: WATER; GLYCERIN; HYDROGEN PEROXIDE

eco HAND SANITIZER LIQUID

Purpose: Antiseptic

INDICATIONS AND USAGE

Use: Hand sanitizer to help reduce bacteria on skin

DOSAGE AND ADMINISTRATION

Directions for Use: Supervise children when they use this product. For occasional and personal domestic use. Rub thoroughly into hands for at least 30 seconds. Allow to dry.

ACTIVE INGREDIENT

Medicinal Ingredients: Ethyl Alcohol* (80% v/v).

INACTIVE INGREDIENT

Ingredients: Aqua, Glycerin*, Hydrogen Peroxide*.

WARNINGS

Warning: For external use only. Flammable. Keep away from open flame and sources of heat. Avoid contact with eyes. Should this occur, flush eyes with water. If irritation develops, discontinue use and contact a health care practitioner.

Contraindications: Do not use on children/infants less than 2 years of age (unless directed by a health care practitioner).

Keep out of reach of children.

STORAGE AND HANDLING

Store between 15° C/59° F and 30° C/86° F

kills 99.9% of germs

Get your hands on it !

Fragrance free | Hypoallergenic

Enriched Liquid with Glycerin | Can be used as is or as a refill

Made in Canada from Domestic and imported products.

Eco Sanitizer | ecosanitizer.ca